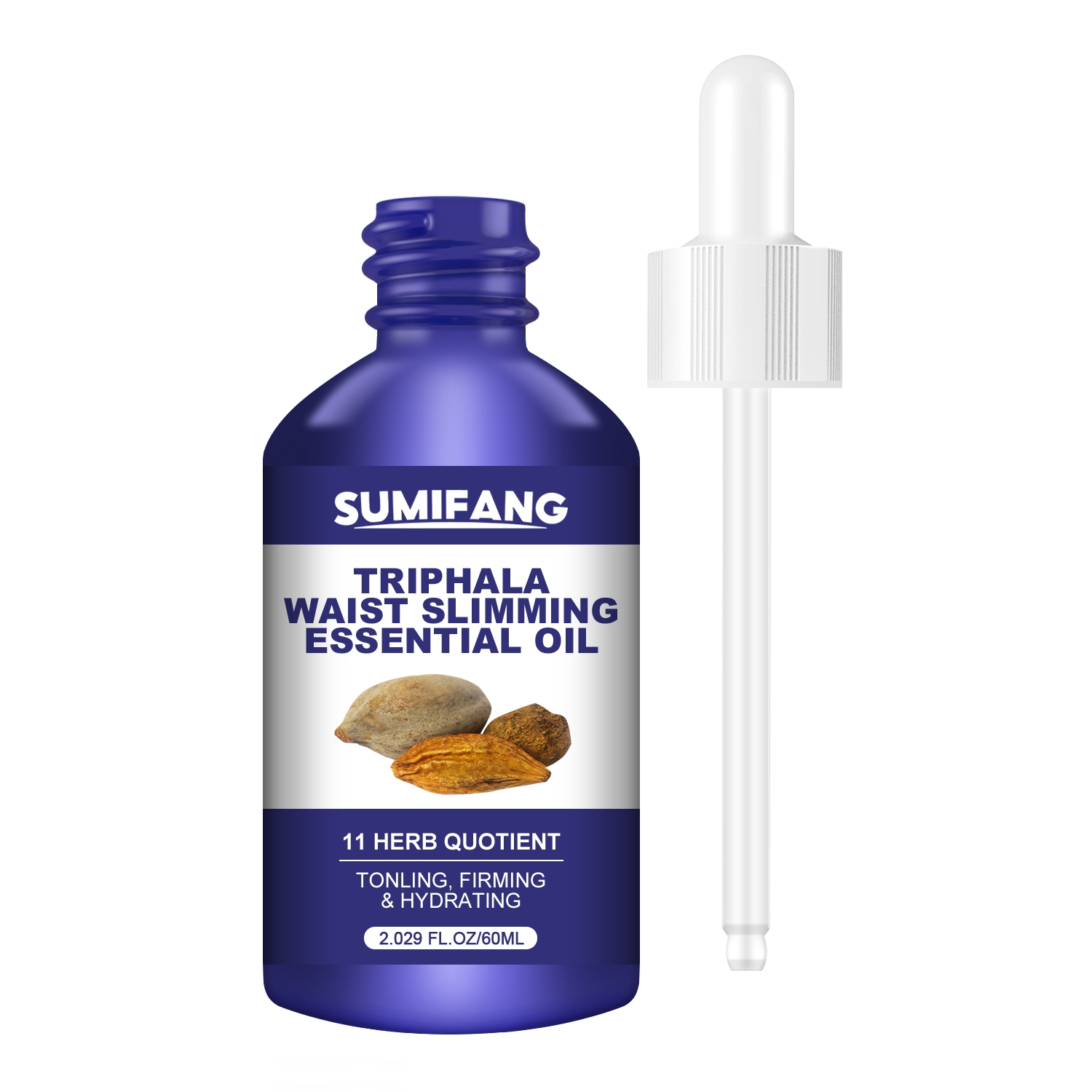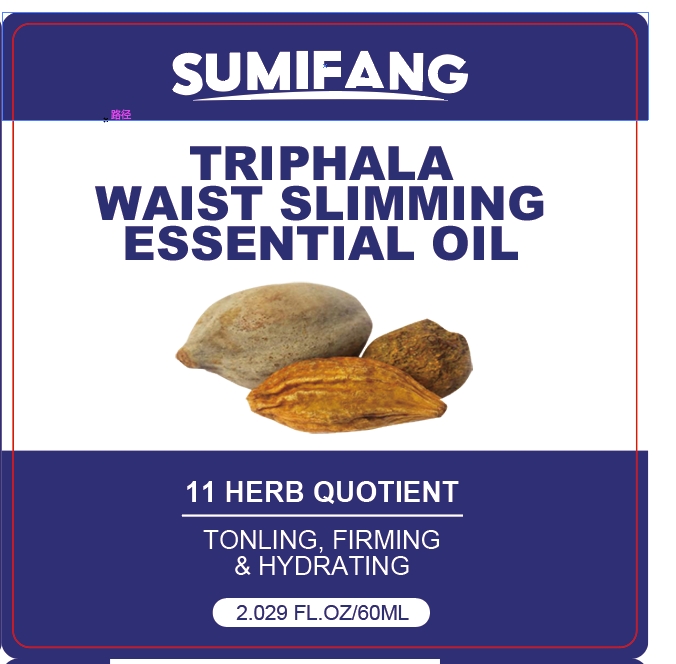 DRUG LABEL: Essential Oil
NDC: 84025-103 | Form: OIL
Manufacturer: Guangzhou Yanxi Biotechnology Co.. Ltd
Category: otc | Type: HUMAN OTC DRUG LABEL
Date: 20240731

ACTIVE INGREDIENTS: ALLANTOIN 3 mg/60 mL; 1,2-BUTANEDIOL 5 mg/60 mL
INACTIVE INGREDIENTS: WATER

DOSAGE AND ADMINISTRATION

Essential oils for daily skin massage and care

WARNINGS

Keep out of children

INACTIVE INGREDIENT

Aqua

INDICATIONS AND USAGE

For daily skin care

Keep out of children

PURPOSE

Moisturizes and cares for the skin